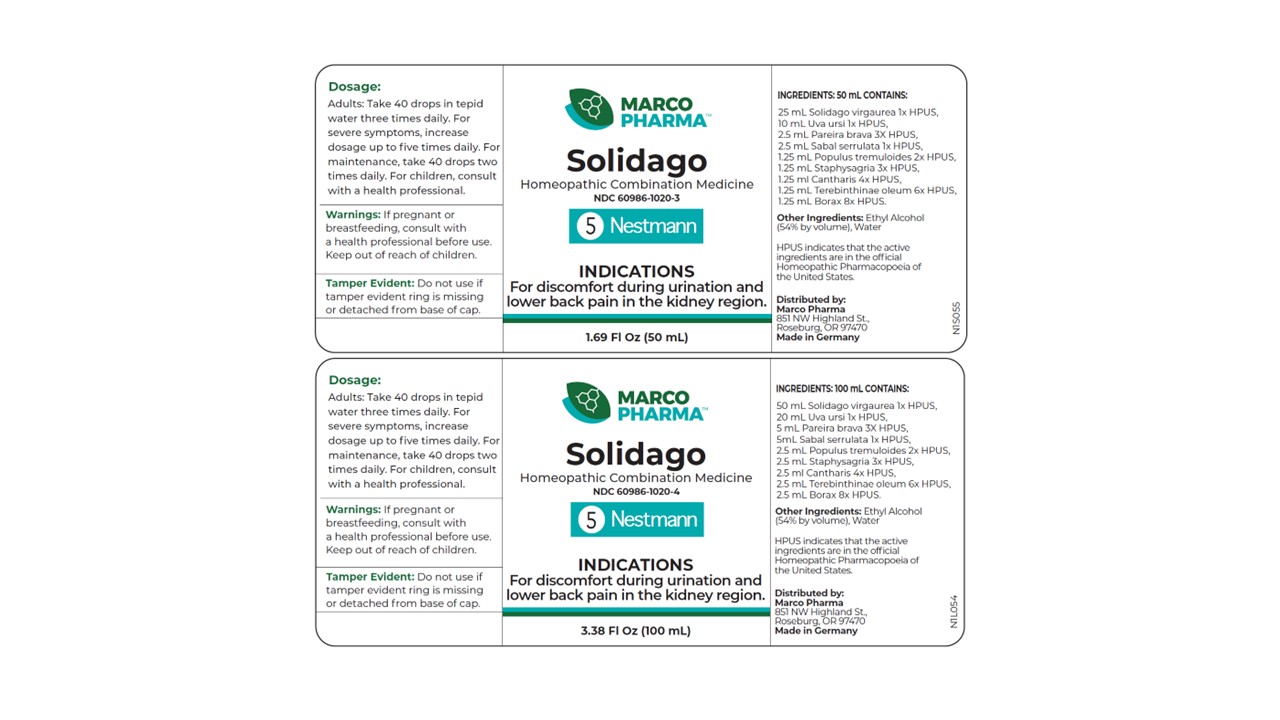 DRUG LABEL: Solidago
NDC: 60986-1020 | Form: LIQUID
Manufacturer: Marco Pharma International LLC.
Category: homeopathic | Type: HUMAN OTC DRUG LABEL
Date: 20260112

ACTIVE INGREDIENTS: SOLIDAGO VIRGAUREA FLOWERING TOP 1 [hp_X]/1 mL; ARCTOSTAPHYLOS UVA-URSI LEAF 1 [hp_X]/1 mL; CHONDRODENDRON TOMENTOSUM ROOT 3 [hp_X]/1 mL; SAW PALMETTO 1 [hp_X]/1 mL; POPULUS TREMULOIDES BARK 2 [hp_X]/1 mL; DELPHINIUM STAPHISAGRIA SEED 3 [hp_X]/1 mL; LYTTA VESICATORIA 4 [hp_X]/1 mL; LARIX DECIDUA RESIN 6 [hp_X]/1 mL; SODIUM BORATE 8 [hp_X]/1 mL
INACTIVE INGREDIENTS: ALCOHOL; WATER

Drug Facts

Active Ingredients

Goldenrod 1x HPUS

Bearberry 1x HPUS

Pareira brava 3x HPUS

Saw Palmetto 1x HPUS

Aspen 2x HPUS

Stavesacre 3x HPUS

Spanish Fly 4x HPUS

Terpentine 6x HPUS

Sodium borate 8x HPUS

The letters HPUS indicates that the components in this product are officially monographed in the Homeopathic Pharmacopoeia of United Sates.

Purpose

For discomfort during urination and lower back pain in the kidney region.

Keep out of reach of children.

Suggested use

Adults: Take 40 drops in tepid water three times daily. For severe symptoms, take 40 drops four to five time daily. After improvement is felt, take 40 drops three times daily. Children receive 1/2 or less of the adult amount.

Warnings

If pregnant or breast-feeding, consult a health professional before use.

DOSAGE AND ADMINISTRATION

(Read Suggested Use Section)

Inactive Ingredients

Ethyl Alcohol (54% by vol.) and Water